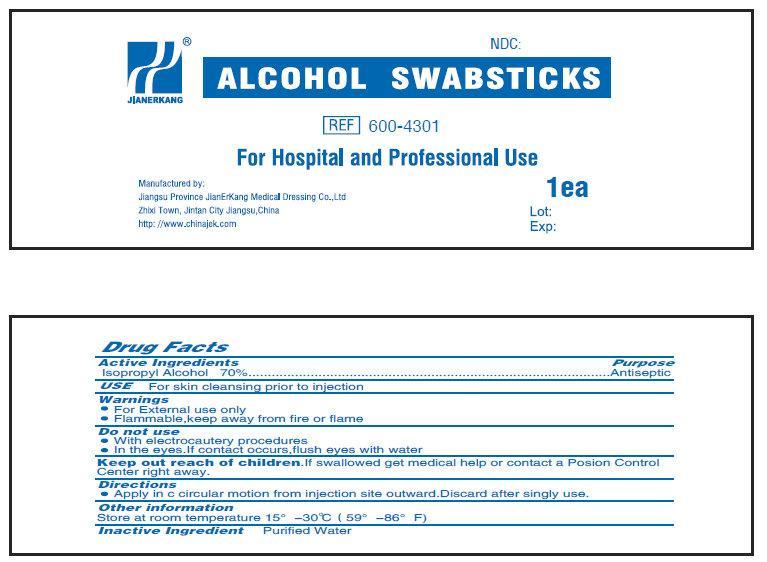 DRUG LABEL: Alcohol
NDC: 34645-1042 | Form: SWAB
Manufacturer: Jianerkang Medical Co., Ltd
Category: otc | Type: HUMAN OTC DRUG LABEL
Date: 20231022

ACTIVE INGREDIENTS: ISOPROPYL ALCOHOL 70 mL/100 mL
INACTIVE INGREDIENTS: WATER

ALCOHOL SWABSTICK

Active ingredient

Isopropyl Alcohol 70%

Purpose

Antiseptic

Uses

USE For skin cleansing prior to injection.

Warnings

- For external use only.
- Flammable. Keep away from fire or flame.

Do not use

- with electrocautery procedures
- In the eyes. If contact occurs,flush eyes with water

Keep out of reach of children

- condition persists or gets worse or lasts for more than 72 hours

Directions

- Apply in a circular motion from injection site outward.Discard after singly use.

Storage

Store at room temperature 15°-30℃（59°-86°F)

Inactive ingredients

Purified Water